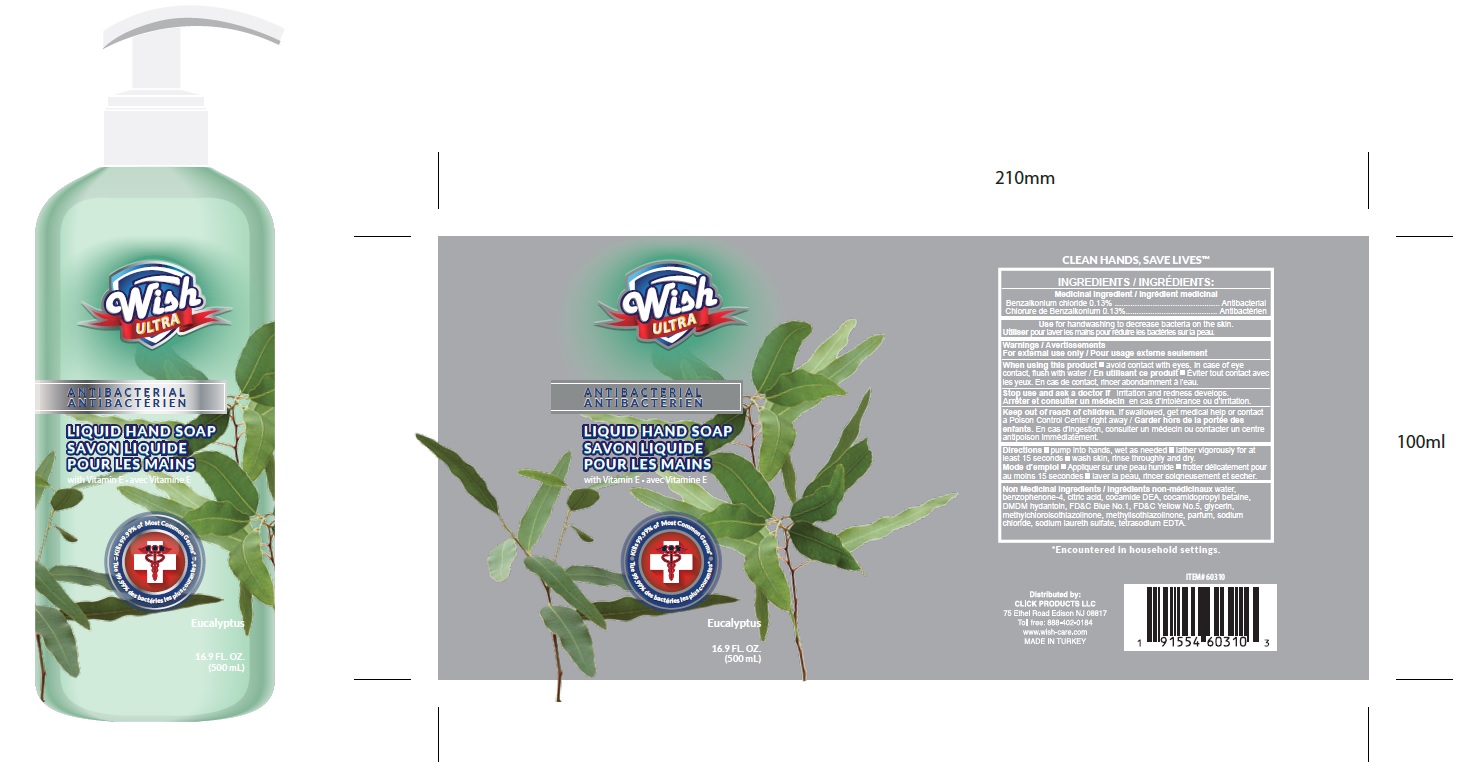 DRUG LABEL: ANTIBACTERIAL HANDWASH
NDC: 71611-070 | Form: LIQUID
Manufacturer: Click Products LLC
Category: otc | Type: HUMAN OTC DRUG LABEL
Date: 20201027

ACTIVE INGREDIENTS: BENZALKONIUM CHLORIDE 0.13 g/100 mL
INACTIVE INGREDIENTS: METHYLCHLOROISOTHIAZOLINONE; METHYLISOTHIAZOLINONE; CITRIC ACID MONOHYDRATE; SODIUM CHLORIDE; WATER; SODIUM LAURETH-3 SULFATE; COCAMIDOPROPYL BETAINE; COCO DIETHANOLAMIDE; DMDM HYDANTOIN; FD&C BLUE NO. 1; GLYCERIN; EDETATE SODIUM; SULISOBENZONE; FD&C YELLOW NO. 5; BENZYL ALCOHOL

Wish ULTRA ANTIBACTERIAL LIQUID HAND SOAP - Eucalyptus

Active Ingredient

Benzalkonium Chloride 0.13%

Purpose

Antibacterial

USES

- For Handwashing to decrease bacteria on the skin

WARNING

For external use only.

WHEN USING

- avoid contact with eyes.
- In case of eye contact, flush with water

Stop use and ask a doctor if

- If irritation and redness develops.

KEEP OUT OF REACH OF CHILDREN.

If swallowed, get medical help or contact a Poison Control Center immediately.

DIRECTIONS

- Pump into hands ,wet as needed
- lather vigorously for at least 15 seconds
- Wash skin, rinse throughly and dry.

Inactive Ingredients:

Water（Aqua),Cocamidopropyl Betaine,Sodium Chloride,Fragrance, Citric Acid,Methylchloroisothiazolinone,Methylisothiazolinone, Cocamide/DEA, FD&C Blue No1, Glycerin ,Parfum,Tetrasodium EDTA,Sodium laureth sultate.